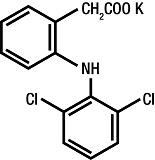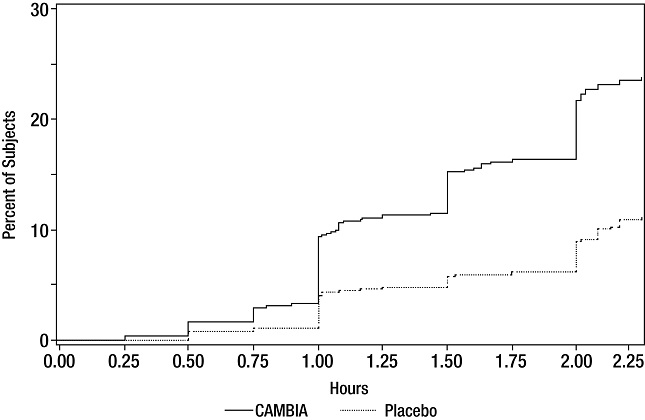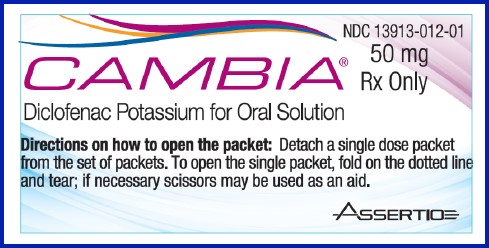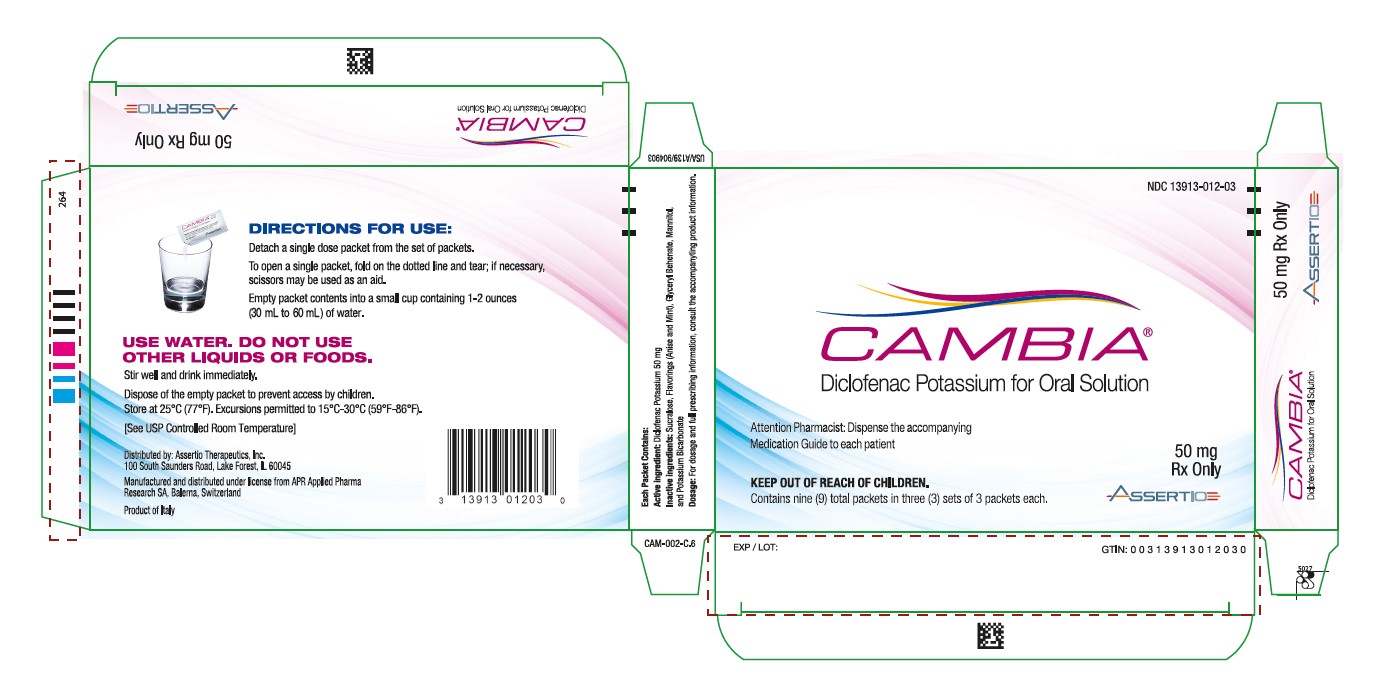 DRUG LABEL: Cambia
NDC: 13913-012 | Form: POWDER, FOR SOLUTION
Manufacturer: Assertio Therapeutics, Inc.
Category: prescription | Type: HUMAN PRESCRIPTION DRUG LABEL
Date: 20241211

ACTIVE INGREDIENTS: DICLOFENAC POTASSIUM  50 mg/1 1
INACTIVE INGREDIENTS: GLYCERYL DIBEHENATE; MANNITOL; POTASSIUM BICARBONATE; SUCRALOSE

HIGHLIGHTS OF PRESCRIBING INFORMATION

These highlights do not include all the information needed to use CAMBIA safely and effectively. See full prescribing information for CAMBIA.
CAMBIA® (diclofenac potassium), for oral solution
Initial U.S. Approval: 1988

WARNING: RISK OF SERIOUS CARDIOVASCULAR AND GASTROINTESTINAL EVENTS

See full prescribing information for complete boxed warning

- Non-steroidal anti-inflammatory drugs (NSAIDs) cause an increased risk of serious cardiovascular thrombotic events, including myocardial infarction and stroke, which can be fatal. This risk may occur early in treatment and may increase with duration of use (5.1)
- CAMBIA is contraindicated in the setting of coronary artery bypass graft (CABG) surgery (4, 5.1)

- NSAIDs cause an increased risk of serious gastrointestinal (GI) adverse events including bleeding, ulceration, and perforation of the stomach or intestines, which can be fatal. These events can occur at any time during use and without warning symptoms. Elderly patients and patients with a prior history of peptic ulcer disease and/or GI bleeding are at greater risk for serious GI events (5.2)

RECENT MAJOR CHANGES

Warnings and Precautions (5.9) | 11/2024

1 INDICATIONS AND USAGE

CAMBIA is a non-steroidal anti-inflammatory drug (NSAID) indicated for the acute treatment of migraine attacks with or without aura in adults 18 years of age or older (1)

Limitations of Use (1):

- CAMBIA is not indicated for the prophylactic therapy of migraine
- Safety and effectiveness of CAMBIA not established for cluster headache, which is present in an older, predominantly male population

2 DOSAGE AND ADMINISTRATION

Single 50 mg dose; mix single packet contents with 1 to 2 ounces (30 to 60 mL) of water prior to administration

- Use the lowest effective dose for shortest duration consistent with individual patient treatment goals (2.1)

3 DOSAGE FORMS AND STRENGTHS

Packets: Each containing buffered diclofenac potassium 50 mg in a soluble powder (3)

4 CONTRAINDICATIONS

- Known hypersensitivity to diclofenac or NSAIDs or any components of the drug product (4)
- History of asthma, urticaria, or other allergic-type reactions after taking aspirin or other NSAIDs (4)
- In the setting of (CABG) surgery (4)

5 WARNINGS AND PRECAUTIONS

- Hepatotoxicity: Inform patients of warning signs and symptoms of hepatotoxicity. Discontinue if abnormal liver tests persist or worsen or if clinical signs and symptoms of liver disease develop (5.3, 8.6, 12.3)
- Hypertension: Patients taking some antihypertensive medications may have impaired response to these therapies when taking NSAIDs. Monitor blood pressure (5.4, 7)
- Heart Failure and Edema: Avoid use of CAMBIA in patients with severe heart failure unless benefits are expected to outweigh risk of worsening heart failure (5.5)
- Renal Toxicity: Monitor renal function in patients with renal or hepatic impairment, heart failure, dehydration, or hypovolemia. Avoid use of CAMBIA in patients with advanced renal disease unless benefits are expected to outweigh risk of worsening renal function (5.6)
- Anaphylactic Reactions: Seek emergency help if an anaphylactic reaction occurs (5.7)
- Exacerbation of Asthma Related to Aspirin Sensitivity: CAMBIA is contraindicated in patients with aspirin-sensitive asthma. Monitor patients with preexisting asthma (without aspirin sensitivity) (5.8)
- Serious Skin Reactions: Discontinue CAMBIA at first appearance of skin rash or other signs of hypersensitivity (5.9)
- Drug Reaction with Eosinophilia and Systemic Symptoms (DRESS): Discontinue and evaluate clinically (5.10)
- Medication Overuse Headache: Detoxification may be necessary. (5.11)
- Fetal Toxicity: Limit use of NSAIDs, including Cambia, between about 20 to 30 weeks in pregnancy due to the risk of oligohydramnios/fetal renal dysfunction. Avoid use of NSAIDs in women at about 30 weeks gestation and later in pregnancy due to the risks of oligohydramnios/fetal dysfunction and premature closure of the fetal ductus arteriosus (5.12, 8.1)
- Hematologic Toxicity: Monitor hemoglobin or hematocrit in patients with any signs or symptoms of anemia (5.13, 7)

6 ADVERSE REACTIONS

Most common adverse reactions (≥1% and >placebo) were nausea and dizziness (6.1)

To report SUSPECTED ADVERSE REACTIONS, contact Assertio Therapeutics, Inc. at 866-458-6389 or FDA at 1-800-FDA-1088 or www.fda.gov/medwatch.

7 DRUG INTERACTIONS

- Drugs that Interfere with Hemostasis (e.g. warfarin, aspirin, SSRIs/SNRIs): Monitor patients for bleeding who are concomitantly taking CAMBIA with drugs that interfere with hemostasis. Concomitant use of CAMBIA and analgesic doses of aspirin is not generally recommended (7)
- ACE Inhibitors and ARBs: Concomitant use with CAMBIA in elderly, volume depleted, or those with renal impairment may result in deterioration of renal function. In such high risk patients, monitor for signs of worsening renal function (7)
- Diuretics: NSAIDs can reduce natriuretic effect of loop and thiazide diuretics. Monitor patients to assure diuretic efficacy including antihypertensive effects (7)
- Digoxin: Concomitant use with CAMBIA can increase serum concentration and prolong half-life of digoxin. Monitor serum digoxin levels (7)

8 USE IN SPECIFIC POPULATIONS

- Infertility: NSAIDs are associated with reversible infertility. Consider withdrawal of CAMBIA in women who have difficulties conceiving (8.3)

FULL PRESCRIBING INFORMATION

WARNING: RISK OF SERIOUS CARDIOVASCULAR AND GASTROINTESTINAL EVENTS

Cardiovascular Thrombotic Events

- Nonsteroidal anti-inflammatory drugs (NSAIDs) cause an increased risk of serious cardiovascular thrombotic events, including myocardial infarction and stroke, which can be fatal. This risk may occur early in treatment and may increase with duration of use [see Warnings and Precautions (5.1)].
- CAMBIA is contraindicated in the setting of coronary artery bypass graft (CABG) surgery [see Contraindications (4) and Warnings and Precautions (5.1)].

Gastrointestinal Bleeding, Ulceration, and Perforation

- NSAIDs cause an increased risk of serious gastrointestinal (GI) adverse events including bleeding, ulceration, and perforation of the stomach or intestines, which can be fatal. These events can occur at any time during use and without warning symptoms. Elderly patients and patients with a prior history of peptic ulcer disease and/or GI bleeding are at greater risk for serious GI events [see Warnings and Precautions (5.2)].

1 INDICATIONS AND USAGE

CAMBIA is indicated for the acute treatment of migraine attacks with or without aura in adults (18 years of age or older).

Limitations of Use:

- CAMBIA is not indicated for the prophylactic therapy of migraine.
- The safety and effectiveness of CAMBIA have not been established for cluster headache, which is present in an older, predominantly male population.

2 DOSAGE AND ADMINISTRATION

2.1 Acute Treatment of Migraine

Administer one packet (50 mg) of CAMBIA for the acute treatment of migraine. Empty the contents of one packet into a cup containing 1 to 2 ounces (30 to 60 mL) of water, mix well and drink immediately.

Do not use liquids other than water.

Taking CAMBIA with food may cause a reduction in effectiveness compared to taking CAMBIA on an empty stomach [see Clinical Pharmacology (12.3)].

Use the lowest effective dose for the shortest duration consistent with individual patient treatment goals. The safety and effectiveness of a second dose have not been established.

2.2 Non-Interchangeability with Other Formulations of Diclofenac

Different formulations of oral diclofenac (e.g., CAMBIA, diclofenac sodium enteric-coated tablets, diclofenac sodium extended-release tablets, or diclofenac potassium immediate-release tablets) may not be bioequivalent even if the milligram strength is the same. Therefore, it is not possible to convert dosing from any other formulation of diclofenac to CAMBIA.

3 DOSAGE FORMS AND STRENGTHS

CAMBIA is available in individual packets each designed to deliver a 50 mg dose when mixed in water.

4 CONTRAINDICATIONS

CAMBIA is contraindicated in the following patients:

- Known hypersensitivity (e.g., anaphylactic reactions and serious skin reactions) to diclofenac or any components of the drug product [see Warnings and Precautions (5.7, 5.9)]
- History of asthma, urticaria, or other allergic-type reactions after taking aspirin or other NSAIDs. Severe, sometimes fatal, anaphylactic reactions to NSAIDs have been reported in such patients [see Warnings and Precautions (5.7, 5.8)]
- In the setting of coronary artery bypass graft (CABG) surgery [see Warnings and Precautions (5.1)]

5 WARNINGS AND PRECAUTIONS

5.1 Cardiovascular Thrombotic Events

Clinical trials of several COX-2 selective and nonselective NSAIDs of up to three years duration have shown an increased risk of serious cardiovascular (CV) thrombotic events, including myocardial infarction (MI) and stroke, which can be fatal. Based on available data, it is unclear that the risk for CV thrombotic events is similar for all NSAIDs. The relative increase in serious CV thrombotic events over baseline conferred by NSAID use appears to be similar in those with and without known CV disease or risk factors for CV disease. However, patients with known CV disease or risk factors had a higher absolute incidence of excess serious CV thrombotic events, due to their increased baseline rate. Some observational studies found that this increased risk of serious CV thrombotic events began as early as the first weeks of treatment. The increase in CV thrombotic risk has been observed most consistently at higher doses.

To minimize the potential risk for an adverse CV event in NSAID-treated patients, use the lowest effective dose for the shortest duration possible. Physicians and patients should remain alert for the development of such events, throughout the entire treatment course, even in the absence of previous CV symptoms. Patients should be informed about the symptoms of serious CV events and the steps to take if they occur.

There is no consistent evidence that concurrent use of aspirin mitigates the increased risk of serious CV thrombotic events associated with NSAID use. The concurrent use of aspirin and an NSAID, such as diclofenac, increases the risk of serious gastrointestinal (GI) events [see Warnings and Precautions (5.2)].

Status Post Coronary Artery Bypass Graft (CABG) Surgery

Two large, controlled clinical trials of a COX-2 selective NSAID for the treatment of pain in the first 10-14 days following CABG surgery found an increased incidence of myocardial infarction and stroke. NSAIDs are contraindicated in the setting of CABG [see Contraindications (4)].

Post-MI Patients

Observational studies conducted in the Danish National Registry have demonstrated that patients treated with NSAIDs in the post-MI period were at increased risk of reinfarction, CV-related death, and all-cause mortality beginning in the first week of treatment. In this same cohort, the incidence of death in the first year post-MI was 20 per 100 person years in NSAID-treated patients compared to 12 per 100 person years in non-NSAID exposed patients. Although the absolute rate of death declined somewhat after the first year post-MI, the increased relative risk of death in NSAID users persisted over at least the next four years of follow-up.

Avoid the use of CAMBIA in patients with a recent MI unless the benefits are expected to outweigh the risk of recurrent CV thrombotic events. If CAMBIA is used in patients with a recent MI, monitor patients for signs of cardiac ischemia.

5.2 Gastrointestinal Bleeding, Ulceration, and Perforation

NSAIDs, including diclofenac, cause serious gastrointestinal (GI) adverse events including inflammation, bleeding, ulceration, and perforation of the esophagus, stomach, small intestine, or large intestine, which can be fatal. These serious adverse events can occur at any time, with or without warning symptoms, in patients treated with NSAIDs. Only one in five patients who develop a serious upper GI adverse event on NSAID therapy is symptomatic. Upper GI ulcers, gross bleeding, or perforation caused by NSAIDs occurred in approximately 1% of patients treated for 3-6 months, and in about 2%-4% of patients treated for one year. However, even short- term NSAID therapy is not without risk.

Risk Factors for GI Bleeding, Ulceration, and Perforation

Patients with a prior history of peptic ulcer disease and/or GI bleeding who used NSAIDs had a greater than 10-fold increased risk for developing a GI bleed compared to patients without these risk factors. Other factors that increase the risk for GI bleeding in patients treated with NSAIDs include longer duration of NSAID therapy; concomitant use of oral corticosteroids, aspirin, anticoagulants, or selective serotonin reuptake inhibitors (SSRI); smoking; use of alcohol; older age; and poor general health status. Most postmarketing reports of fatal GI events occurred in elderly or debilitated patients. Additionally, patients with advanced liver disease and/or coagulopathy are at increased risk for GI bleeding.

Strategies to Minimize the GI Risk in NSAID-treated patients:

- Use the lowest effective dosage for the shortest possible duration.
- Avoid administration of more than one NSAID at a time.
- Avoid use in patients at higher risk unless benefits are expected to outweigh the increased risk of bleeding. For high risk patients, as well as those with active GI bleeding, consider alternate therapies other than NSAIDs.
- Remain alert for signs and symptoms of GI ulceration and bleeding during NSAID therapy.
- If a serious GI adverse event is suspected, promptly initiate evaluation and treatment, and discontinue CAMBIA until a serious GI adverse event is ruled out.
- In the setting of concomitant use of low-dose aspirin for cardiac prophylaxis, monitor patients more closely for evidence of GI bleeding [see Drug Interactions (7)].

5.3 Hepatotoxicity

Elevations of one or more liver tests may occur during therapy with CAMBIA. These laboratory abnormalities may progress, may persist, or may only be transient with continued therapy. Borderline elevations (less than 3 times the upper limit of the normal [ULN] range) or greater elevations of transaminases occurred in about 15% of diclofenac-treated patients. Of the markers of hepatic function, ALT (SGPT) is recommended for the monitoring of liver injury.

In clinical trials, meaningful elevations (i.e., more than 3 times the ULN) of AST (SGOT) occurred in about 2% of approximately 5,700 patients at some time during treatment (ALT was not measured in all studies). In an open-label, controlled trial of 3,700 patients treated for 2–6 months, patients were monitored at 8 weeks and 1,200 patients were monitored again at 24 weeks. Meaningful elevations of ALT and/or AST occurred in about 4% of the 3,700 patients and included marked elevations (>8 times the ULN) in about 1% of the 3,700 patients. In this open-label study, a higher incidence of borderline (less than 3 times the ULN), moderate (3–8 times the ULN), and marked (>8 times the ULN) elevations of ALT or AST was observed in patients receiving diclofenac when compared to other NSAIDs. Almost all meaningful elevations in transaminases were detected before patients became symptomatic [see Warnings and Precautions (5.15)].

Abnormal tests occurred during the first 2 months of therapy with diclofenac in 42 of the 51 patients in all trials who developed marked transaminase elevations. In postmarketing reports, cases of drug-induced hepatotoxicity have been reported in the first month, and in some cases, the first 2 months of NSAID therapy, but can occur at any time during treatment with diclofenac.

Postmarketing surveillance has reported cases of severe hepatic reactions, including liver necrosis, jaundice, fulminant hepatitis with and without jaundice, and liver failure. Some of these reported cases resulted in fatalities or liver transplantation.

Inform patients of the warning signs and symptoms of hepatotoxicity (e.g., nausea, fatigue, lethargy, diarrhea, pruritus, jaundice, right upper quadrant tenderness, and "flu-like" symptoms). If clinical signs and symptoms consistent with liver disease develop, or if systemic manifestations occur (e.g., eosinophilia, rash, etc.), discontinue CAMBIA immediately, and perform a clinical evaluation of the patient.

To minimize the potential risk for an adverse liver-related event in patients treated with CAMBIA, use the lowest effective dose for the shortest duration possible. Exercise caution when prescribing CAMBIA with concomitant drugs that are known to be potentially hepatotoxic (e.g., acetaminophen, certain antibiotics, antiepileptics). Caution patients to avoid taking nonprescription acetaminophen-containing products while using CAMBIA.

5.4 Hypertension

NSAIDs, including CAMBIA, can lead to new onset of hypertension or worsening of pre-existing hypertension, either of which may contribute to the increased incidence of CV events. Use NSAIDs, including CAMBIA, with caution in patients with hypertension. Monitor blood pressure closely during the initiation of NSAID treatment and throughout the course of therapy.

Patients taking angiotensin converting enzyme (ACE) inhibitors, thiazides, or loop diuretics may have impaired response to these therapies when taking NSAIDs [see Drug Interactions (7)].

5.5 Heart Failure and Edema

The Coxib and traditional NSAID Trialists’ Collaboration meta-analysis of randomized controlled trials demonstrated an approximately two-fold increase in hospitalizations for heart failure in COX-2 selective-treated patients and nonselective NSAID-treated patients compared to placebo-treated patients. In a Danish National Registry study of patients with heart failure, NSAID use increased the risk of MI, hospitalization for heart failure, and death.

Additionally, fluid retention and edema have been observed in some patients treated with NSAIDs. Use of diclofenac may blunt the CV effects of several therapeutic agents used to treat these medical conditions (e.g., diuretics, ACE inhibitors, or angiotensin receptor blockers [ARBs]) [see Drug Interactions (7)].

Avoid the use of CAMBIA in patients with severe heart failure unless the benefits are expected to outweigh the risk of worsening heart failure. If CAMBIA is used in patients with severe heart failure, monitor patients for signs of worsening heart failure.

5.6 Renal Toxicity and Hyperkalemia

Renal Toxicity

Long-term administration of NSAIDs has resulted in renal papillary necrosis and other renal injury. Renal toxicity has also been seen in patients in whom renal prostaglandins have a compensatory role in the maintenance of renal perfusion. In these patients, administration of an NSAID may cause a dose-dependent reduction in prostaglandin formation and, secondarily, in renal blood flow, which may precipitate overt renal decompensation. Patients at greatest risk of this reaction are those with impaired renal function, dehydration, hypovolemia, heart failure, liver dysfunction, those taking diuretics and ACE inhibitors or ARBs, and the elderly. Discontinuation of NSAID therapy is usually followed by recovery to the pretreatment state.

No information is available from controlled clinical studies regarding the use of CAMBIA in patients with advanced renal disease. The renal effects of CAMBIA may hasten the progression of renal dysfunction in patients with pre-existing renal disease.

Correct volume status in dehydrated or hypovolemic patients prior to initiating CAMBIA. Monitor renal function in patients with renal or hepatic impairment, heart failure, dehydration, or hypovolemia during use of CAMBIA [see Drug Interactions (7)]. Avoid the use of CAMBIA in patients with advanced renal disease unless the benefits are expected to outweigh the risk of worsening renal function. If CAMBIA is used in patients with advanced renal disease, monitor patients for signs of worsening renal function.

Hyperkalemia

Increases in serum potassium concentration, including hyperkalemia, have been reported with use of NSAIDs, even in some patients without renal impairment. In patients with normal renal function, these effects have been attributed to a hyporeninemic-hypoaldosteronism state.

5.7 Anaphylactic Reactions

Diclofenac has been associated with anaphylactic reactions in patients with and without known hypersensitivity to diclofenac and in patients with aspirin-sensitive asthma [see Contraindications (4) and Warnings and Precautions (5.8)].

Seek emergency help if an anaphylactic reaction occurs.

5.8 Exacerbation of Asthma Related to Aspirin Sensitivity

A subpopulation of patients with asthma may have aspirin-sensitive asthma which may include chronic rhinosinusitis complicated by nasal polyps; severe, potentially fatal bronchospasm; and/or intolerance to aspirin and other NSAIDs. Because cross-reactivity between aspirin and other NSAIDs has been reported in such aspirin-sensitive patients, CAMBIA is contraindicated in patients with this form of aspirin sensitivity [see Contraindications (4)]. When CAMBIA is used in patients with preexisting asthma (without known aspirin sensitivity), monitor patients for changes in the signs and symptoms of asthma.

5.9 Serious Skin Reactions

NSAIDs, including diclofenac, can cause serious skin adverse reactions such as exfoliative dermatitis, Stevens-Johnson Syndrome (SJS), and toxic epidermal necrolysis (TEN), which can be fatal. NSAIDs can also cause fixed drug eruption (FDE). FDE may present as a more severe variant known as generalized bullous fixed drug eruption (GBFDE), which can be life-threatening. These serious events may occur without warning. Inform patients about the signs and symptoms of serious skin reactions, and to discontinue the use of CAMBIA at the first appearance of skin rash or any other sign of hypersensitivity. CAMBIA is contraindicated in patients with previous serious skin reactions to NSAIDs [see Contraindications (4)].

5.10 Drug Reaction with Eosinophilia and Systemic Symptoms (DRESS)

Drug Reaction with Eosinophilia and Systemic Symptoms (DRESS) has been reported in patients taking NSAIDs such as CAMBIA. Some of these events have been fatal or life-threatening. DRESS typically, although not exclusively, presents with fever, rash, lymphadenopathy, and/or facial swelling. Other clinical manifestations may include hepatitis, nephritis, hematological abnormalities, myocarditis, or myositis. Sometimes symptoms of DRESS may resemble an acute viral infection. Eosinophilia is often present. Because this disorder is variable in its presentation, other organ systems not noted here may be involved. It is important to note that early manifestations of hypersensitivity, such as fever or lymphadenopathy, may be present even though rash is not evident. If such signs or symptoms are present, discontinue CAMBIA and evaluate the patient immediately.

5.11 Medication Overuse Headache

Overuse of acute migraine drugs (e.g., ergotamine, triptans, opioids, nonsteroidal anti-inflammatory drugs or combination of these drugs for 10 or more days per month) may lead to exacerbation of headache (medication overuse headache). Medication overuse headache may present as migraine-like daily headaches or as a marked increase in frequency of migraine attacks. Detoxification of patients, including withdrawal of the overused drugs and treatment of withdrawal symptoms (which often includes a transient worsening of headache) may be necessary.

5.12 Fetal Toxicity

Premature Closure of Fetal Ductus Arteriosus

Avoid use of NSAIDs, including CAMBIA, in pregnant women at about 30 weeks gestation and later. NSAIDs, including CAMBIA, increase the risk of premature closure of the fetal ductus arteriosus at approximately this gestational age.

Oligohydramnios/Neonatal Renal Impairment

Use of NSAIDs, including CAMBIA, at about 20 weeks gestation or later in pregnancy may cause fetal renal dysfunction leading to oligohydramnios and, in some cases, neonatal renal impairment. These adverse outcomes are seen, on average, after days to weeks of treatment, although oligohydramnios has been infrequently reported as soon as 48 hours after NSAID initiation.

Oligohydramnios is often, but not always, reversible with treatment discontinuation. Complications of prolonged oligohydramnios may, for example, include limb contractures and delayed lung maturation. In some postmarketing cases of impaired neonatal renal function, invasive procedures such as exchange transfusion or dialysis were required.

If NSAID treatment is necessary between about 20 weeks and 30 weeks gestation, limit CAMBIA use to the lowest effective dose and shortest duration possible. Consider ultrasound monitoring of amniotic fluid if CAMBIA treatment extends beyond 48 hours. Discontinue CAMBIA if oligohydramnios occurs and follow up according to clinical practice [see Use in Specific Population (8.1)].

5.13 Hematologic Toxicity

Anemia has occurred in NSAID-treated patients. This may be due to occult or gross blood loss, fluid retention, or an incompletely described effect upon erythropoiesis. If a patient treated with CAMBIA has any signs or symptoms of anemia, monitor hemoglobin or hematocrit.

NSAIDs, including CAMBIA, may increase the risk of bleeding events. Concomitant use of warfarin and other anticoagulants, antiplatelet agents (e.g., aspirin), and serotonin reuptake inhibitors (SSRIs) and serotonin norepinephrine reuptake inhibitors (SNRIs) may increase this risk. Monitor these patients and any patient who may be adversely affected by alterations in platelet function for signs of bleeding [see Drug Interactions (7)].

5.14 Masking of Inflammation and Fever

The pharmacological activity of CAMBIA in reducing inflammation, and possibly fever, may diminish the utility of diagnostic signs in detecting infections.

5.15 Laboratory Monitoring

Because serious GI bleeding, hepatotoxicity, and renal injury can occur without warning symptoms or signs, consider monitoring patients on long-term NSAID treatment with a CBC and a chemistry profile periodically [see Warnings and Precautions (5.2, 5.3, 5.6)].

Discontinue CAMBIA if abnormal liver tests or renal tests persist or worsen.

6 ADVERSE REACTIONS

The following serious adverse reactions are discussed in greater detail in other sections of the labeling:

- Cardiovascular Thrombotic Events [see Warnings and Precautions (5.1)]
- GI Bleeding, Ulceration and Perforation [see Warnings and Precautions (5.2)]
- Hepatotoxicity [see Warnings and Precautions (5.3)]
- Hypertension [see Warnings and Precautions (5.4)]
- Heart Failure and Edema [see Warnings and Precautions (5.5)]
- Renal Toxicity and Hyperkalemia [see Warnings and Precautions (5.6)]
- Anaphylactic Reactions [see Warnings and Precautions (5.7)]
- Serious Skin Reactions [see Warnings and Precautions (5.9)]
- Drug Reaction with Eosinophilia and Systemic Symptoms (DRESS) [see Warnings and Precautions (5.10)]
- Medication Overuse Headache [see Warnings and Precautions (5.11)]
- Hematologic Toxicity [see Warnings and Precautions (5.13)]

6.1 Clinical Trials Experience

Because clinical trials are conducted under widely varying conditions, adverse reaction rates observed in the clinical trials of a drug cannot be directly compared with rates in the clinical trials of another drug and may not reflect the rates observed in practice.

The safety of a single dose of CAMBIA was evaluated in 2 placebo-controlled trials with a total of 634 migraine patients treated with CAMBIA for a single migraine headache. Following treatment with diclofenac potassium (either CAMBIA or diclofenac potassium immediate-release tablets [as a control]), 5 subjects (0.8%) withdrew from the studies; following placebo exposure, 1 subject (0.2%) withdrew.

The most common adverse reactions (i.e., that occurred in 1% or more of CAMBIA-treated patients) and more frequent with CAMBIA than with placebo were nausea and dizziness (see Table 1).

Table 1: Adverse Reactions With Incidence >1% and Greater Than Placebo in Studies 1 and 2 Combined
Adverse Reactions | CAMBIA N=634 | Placebo N=646
Gastrointestinal
Nausea | 3% | 2%
Nervous System
Dizziness | 1% | 0.5%

The most common adverse events resulting in discontinuation of patients following CAMBIA dosing in controlled clinical trials were urticaria (0.2%) and flushing (0.2%). No withdrawals were due to a serious reaction.

6.2 Postmarketing Experience

The following adverse reactions have been identified during post approval use of diclofenac or other NSAIDs. Because these reactions are reported voluntarily from a population of uncertain size, it is not always possible to reliably estimate their frequency or establish a causal relationship to drug exposure.

Adverse Reactions Reported With Diclofenac and Other NSAIDs

In patients taking diclofenac or other NSAIDs, the most frequently reported adverse reactions occurring in approximately 1%-10% of patients are: GI reactions (including abdominal pain, constipation, diarrhea, dyspepsia, flatulence, gross bleeding/perforation, heartburn, nausea, GI ulcers [gastric/duodenal], and vomiting), abnormal renal function, anemia, dizziness, edema, elevated liver enzymes, headaches, increased bleeding time, pruritus, rashes, and tinnitus.

Other less frequently occurring adverse reactions identified during post approval use of diclofenac and other NSAIDs include fixed drug eruption [see Warnings and Precautions (5.9)].

Additional adverse reactions reported in patients taking NSAIDs include occasionally:

Body as a Whole: Fever, infection, sepsis

Cardiovascular System: Congestive heart failure, hypertension, tachycardia, syncope

Digestive System: Dry mouth, esophagitis, gastric/peptic ulcers, gastritis, gastrointestinal bleeding, glossitis, hematemesis, hepatitis, jaundice

Hemic and Lymphatic System: Ecchymosis, eosinophilia, leukopenia, melena, purpura, rectal bleeding, stomatitis, thrombocytopenia

Metabolic and Nutritional: Weight changes

Nervous System: Anxiety, asthenia, confusion, depression, dream abnormalities, drowsiness, insomnia, malaise, nervousness, paresthesia, somnolence, tremors, vertigo

Respiratory System: Asthma, dyspnea

Skin and Appendages: Alopecia, photosensitivity, sweating increased

Special Senses: Blurred vision

Urogenital System: Cystitis, dysuria, hematuria, interstitial nephritis, oliguria/polyuria, proteinuria, renal failure

Other adverse reactions in patients taking NSAIDs, which occur rarely, are:

Body as a Whole: Anaphylactic reactions, appetite changes, death

Cardiovascular System: Arrhythmia, hypotension, myocardial infarction, palpitations, vasculitis

Digestive System: Colitis, eructation, liver failure, pancreatitis

Hemic and Lymphatic System: Agranulocytosis, hemolytic anemia, aplastic anemia, lymphadenopathy, pancytopenia

Metabolic and Nutritional: Hyperglycemia

Nervous System: Convulsions, coma, hallucinations, meningitis

Respiratory System: Respiratory depression, pneumonia

Skin and Appendages: Angioedema, toxic epidermal necrolysis, erythema multiforme, exfoliative dermatitis, Stevens-Johnson syndrome

[see Warnings and Precautions (5.9)], urticaria

Special Senses: Conjunctivitis, hearing impairment

7 DRUG INTERACTIONS

See Table 2 for clinically significant drug interactions with diclofenac.

Table 2: Clinically Significant Drug Interactions with Diclofenac
Drugs That Interfere with Hemostasis
Clinical Impact: | - Diclofenac and anticoagulants such as warfarin have a synergistic effect on bleeding. The concomitant use of diclofenac and anticoagulants have an increased risk of serious bleeding compared to the use of either drug alone. - Serotonin release by platelets plays an important role in hemostasis. Case- control and cohort epidemiological studies showed that concomitant use of drugs that interfere with serotonin reuptake and an NSAID may potentiate the risk of bleeding more than an NSAID alone.
Intervention: | Monitor patients with concomitant use of CAMBIA with anticoagulants (e.g., warfarin), antiplatelet agents (e.g., aspirin), selective serotonin reuptake inhibitors (SSRIs), and serotonin norepinephrine reuptake inhibitors (SNRIs) for signs of bleeding [see Warnings and Precautions (5.13)]
Aspirin
Clinical Impact: | Controlled clinical studies showed that the concomitant use of NSAIDs and analgesic doses of aspirin does not produce any greater therapeutic effect than the use of NSAIDs alone. In a clinical study, the concomitant use of an NSAID and aspirin was associated with a significantly increased incidence of GI adverse reactions as compared to use of the NSAID alone [see Warnings and Precautions (5.2) and Clinical Pharmacology (12.3)].
Intervention: | Concomitant use of CAMBIA and analgesic doses of aspirin is not generally recommended because of the increased risk of bleeding [see Warnings and Precautions (5.13)].
ACE Inhibitors, Angiotensin Receptor Blockers, and Beta-blockers
Clinical Impact: | - NSAIDs may diminish the antihypertensive effect of angiotensin converting enzyme (ACE) inhibitors, angiotensin receptor blockers (ARBs), or beta- blockers (including propranolol). - In patients who are elderly, volume-depleted (including those on diuretic therapy), or have renal impairment, co-administration of an NSAID with ACE inhibitors or ARBs may result in deterioration of renal function, including possible acute renal failure. These effects are usually reversible.
Intervention: | - During concomitant use of CAMBIA and ACE-inhibitors, ARBs, or beta-blockers, monitor blood pressure to ensure that the desired blood pressure is obtained. - During concomitant use of CAMBIA and ACE-inhibitors or ARBs in patients who are elderly, volume-depleted, or have impaired renal function, monitor for signs of worsening renal function [see Warnings and Precautions (5.6)].
Diuretics
Clinical Impact: | Clinical studies, as well as post-marketing observations, showed that NSAIDs reduced the natriuretic effect of loop diuretics (e.g., furosemide) and thiazide diuretics in some patients. This effect has been attributed to the NSAID inhibition of renal prostaglandin synthesis.
Intervention: | During concomitant use of CAMBIA with diuretics, observe patients for signs of worsening renal function, in addition to assuring diuretic efficacy including antihypertensive effects [see Warnings and Precautions (5.6)].
Digoxin
Clinical Impact: | The concomitant use of diclofenac with digoxin has been reported to increase the serum concentration and prolong the half-life of digoxin.
Intervention: | During concomitant use of CAMBIA and digoxin, monitor serum digoxin levels.
Lithium
Clinical Impact: | NSAIDs have produced elevations in plasma lithium levels and reductions in renal lithium clearance. The mean minimum lithium concentration increased 15%, and the renal clearance decreased by approximately 20%. This effect has been attributed to NSAID inhibition of renal prostaglandin synthesis.
Intervention: | During concomitant use of CAMBIA and lithium, monitor patients for signs of lithium toxicity.
Methotrexate
Clinical Impact: | Concomitant use of NSAIDs and methotrexate may increase the risk for methotrexate toxicity (e.g., neutropenia, thrombocytopenia, renal dysfunction).
Intervention: | During concomitant use of CAMBIA and methotrexate, monitor patients for methotrexate toxicity.
Cyclosporine
Clinical Impact: | Concomitant use of CAMBIA and cyclosporine may increase cyclosporine’s nephrotoxicity.
Intervention: | During concomitant use of CAMBIA and cyclosporine, monitor patients for signs of worsening renal function.
NSAIDs and Salicylates
Clinical Impact: | Concomitant use of diclofenac with other NSAIDs or salicylates (e.g., diflunisal, salsalate) increases the risk of GI toxicity, with little or no increase in efficacy [see Warnings and Precautions (5.2)].
Intervention: | The concomitant use of diclofenac with other NSAIDs or salicylates is not recommended.
Pemetrexed
Clinical Impact: | Concomitant use of CAMBIA and pemetrexed may increase the risk of pemetrexed-associated myelosuppression, renal, and GI toxicity (see the pemetrexed prescribing information).
Intervention: | During concomitant use of NSAIDs and pemetrexed, in patients with renal impairment whose creatinine clearance ranges from 45 to 79 mL/min, monitor for myelosuppression, renal and GI toxicity.; NSAIDs with short elimination half-lives (e.g., diclofenac, indomethacin) should be avoided for a period of two days before, the day of, and two days following administration of pemetrexed.; In the absence of data regarding potential interaction between pemetrexed and NSAIDs with longer half-lives (e.g., meloxicam, nabumetone), patients taking these NSAIDs should interrupt dosing for at least five days before, the day of, and two days following pemetrexed administration.
Inhibitors of Cytochrome P450 2C9
Clinical Impact: | Diclofenac is metabolized predominantly by Cytochrome P-450 CYP2C9. Co- administration of medications that inhibit CYP2C9 may affect the pharmacokinetics of diclofenac [see Clinical Pharmacology (12.3)]
Intervention: | During concomitant use of CAMBIA and drugs that inhibit CYP2C9, an increase in the duration between CAMBIA doses for subsequent migraine attacks may be necessary.

8 USE IN SPECIFIC POPULATIONS

8.1 Pregnancy

Risk Summary

Use of NSAIDs, including CAMBIA, can cause premature closure of the fetal ductus arteriosus and fetal renal dysfunction leading to oligohydramnios and, in some cases, neonatal renal impairment. Because of these risks, limit dose and duration of CAMBIA use between about 20 and 30 weeks of gestation, and avoid CAMBIA use at about 30 weeks of gestation and later in pregnancy (see Clinical Considerations, Data).

Premature Closure of Fetal Ductus Arteriosus

Use of NSAIDs, including CAMBIA, at about 30 weeks gestation or later in pregnancy increases the risk
of premature closure of the fetal ductus arteriosus.

Oligohydramnios/Neonatal Renal Impairment

Use of NSAIDs at about 20 weeks gestation or later in pregnancy has been associated with cases of fetal renal dysfunction leading to oligohydramnios, and in some cases, neonatal renal impairment.

Data from observational studies regarding other potential embryofetal risks of NSAID use in women in the first or second trimesters of pregnancy are inconclusive. In animal studies, oral administration of diclofenac sodium to pregnant mice, rats, and rabbits resulted in adverse effects on development (embryofetal mortality, reduced fetal growth) at doses similar to those used clinically. Based on animal data, prostaglandins have been shown to have an important role in endometrial vascular permeability, blastocyst implantation, and decidualization. In animal studies, administration of prostaglandin synthesis inhibitors such as diclofenac potassium, resulted in increased pre- and post-implantation loss. Prostaglandins also have been shown to have an important role in fetal kidney development. In published animal studies, prostaglandin synthesis inhibitors have been reported to impair kidney development when administered at clinically relevant doses.

All pregnancies have a background risk of birth defects, loss, or other adverse outcomes. In the U.S. general population, the estimated background risk of major birth defects and miscarriage in clinically recognized pregnancies is 2-4% and 15-20%, respectively. The reported rate of major birth defects among deliveries to women with migraine ranged from 2.2% to 2.9% and the reported rate of miscarriage was 17%, which were similar to rates reported in women without migraine.

Clinical Considerations

Disease-Associated Maternal and/or Embryo/Fetal Risk

Several studies have suggested that women with migraine may be at increased risk of preeclampsia and gestational hypertension during pregnancy.

Fetal/Neonatal Adverse Reactions

Premature Closure of Fetal Ductus Arteriosus:

Avoid use of NSAIDs in women at about 30 weeks gestation and later in pregnancy, because NSAIDs, including CAMBIA, can cause premature closure of the fetal ductus arteriosus (see Data).

Oligohydramnios/Neonatal Renal Impairment:

If an NSAID is necessary at about 20 weeks gestation or later in pregnancy, limit the use to the lowest effective dose and shortest duration possible. If CAMBIA treatment extends beyond 48 hours, consider monitoring with ultrasound for oligohydramnios. If oligohydramnios occurs, discontinue CAMBIA and follow up according to clinical practice (see Data).

Labor or Delivery

The effects of CAMBIA on labor and delivery in pregnant women are unknown. In rat studies, maternal exposure to NSAIDs, as with other drugs known to inhibit prostaglandin synthesis, increased the incidence of dystocia, delayed parturition, and decreased pup survival.

Data

Human Data

Premature Closure of Fetal Ductus Arteriosus:

Published literature reports that the use of NSAIDs at about 30 weeks of gestation and later in pregnancy may cause premature closure of the fetal ductus arteriosus.

Oligohydramnios/Neonatal Renal Impairment:

Published studies and postmarketing reports describe maternal NSAID use at about 20 weeks gestation or later in pregnancy associated with fetal renal dysfunction leading to oligohydramnios, and in some cases, neonatal renal impairment. These adverse outcomes are seen, on average, after days to weeks of treatment, although oligohydramnios has been infrequently reported as soon as 48 hours after NSAID initiation. In many cases, but not all, the decrease in amniotic fluid was transient and reversible with cessation of the drug. There have been a limited number of case reports of maternal NSAID use and neonatal renal dysfunction without oligohydramnios, some of which were irreversible. Some cases of neonatal renal dysfunction required treatment with invasive procedures, such as exchange transfusion or dialysis.
Methodological limitations of these postmarketing studies and reports include lack of a control group; limited information regarding dose, duration, and timing of drug exposure; and concomitant use of other medications. These limitations preclude establishing a reliable estimate of the risk of adverse fetal and neonatal outcomes with maternal NSAID use. Because the published safety data on neonatal outcomes involved mostly preterm infants, the generalizability of certain reported risks to the full-term infant exposed to NSAIDs through maternal use is uncertain.

Animal Data

Oral administration of diclofenac sodium to pregnant mice and rabbits during organogenesis resulted in embryofetal toxicity at oral doses of up to 20 and 10 mg/kg/day (up to approximately 2 and 4 times, respectively, the recommended human dose [RHD] of 50 mg/day, based on body surface area [mg/m^2]). In rats, oral administration of diclofenac at doses of up to 10 mg/kg/day (up to approximately 2 times the RHD on a mg/m^2 basis) during organogenesis resulted in increased embryofetal mortality and reduced fetal body weights.

8.2 Lactation

Risk Summary

Data from published literature reports with oral preparations of diclofenac indicate the presence of small amounts of diclofenac in human milk. There are no data on the effects on the breastfed infant, or the effects on milk production. The developmental and health benefits of breastfeeding should be considered along with the mother’s clinical need for CAMBIA and any potential adverse effects on the breastfed infant from CAMBIA or from the underlying maternal condition.

8.3 Females and Males of Reproductive Potential

Infertility

Females

Based on the mechanism of action, the use of prostaglandin-mediated NSAIDs, including CAMBIA, may delay or prevent rupture of ovarian follicles, which has been associated with reversible infertility in some women. Published animal studies have shown that administration of prostaglandin synthesis inhibitors has the potential to disrupt prostaglandin-mediated follicular rupture required for ovulation. Small studies in women treated with NSAIDs have also shown a reversible delay in ovulation. Consider withdrawal of NSAIDs, including CAMBIA, in women who have difficulties conceiving or who are undergoing investigation of infertility.

8.4 Pediatric Use

Safety and effectiveness in pediatric patients have not been established.

8.5 Geriatric Use

Elderly patients, compared to younger patients, are at greater risk for NSAID-associated serious cardiovascular, gastrointestinal, and/or renal adverse reactions. If the anticipated benefit for the elderly patient outweighs these potential risks, monitor patients for adverse effects [see Warnings and Precautions (5.1, 5.2, 5.3, 5.6, 5.15)].

Clinical studies of CAMBIA did not include sufficient numbers of subjects aged 65 and over to determine whether they respond differently from younger subjects.

8.6 Hepatic Impairment

Because hepatic metabolism accounts for almost 100% of diclofenac elimination, patients with hepatic impairment should be considered for treatment with CAMBIA only if the benefits outweigh the risks. There is insufficient information available to support dosing recommendations for CAMBIA in patients with hepatic insufficiency [see Clinical Pharmacology (12.3)].

8.7 Renal Impairment

No information is available from controlled clinical studies regarding the use of CAMBIA in patients with advanced renal disease. Therefore, treatment with CAMBIA is not recommended in patients with advanced renal disease. If CAMBIA therapy must be initiated, close monitoring of the patient’s renal function is advisable.

10 OVERDOSAGE

Symptoms following acute NSAID overdoses have been typically limited to lethargy, drowsiness, nausea, vomiting, and epigastric pain, which have been generally reversible with supportive care. Gastrointestinal bleeding has occurred. Hypertension, acute renal failure, respiratory depression and, coma have occurred, but were rare [see Warnings and Precautions (5.1, 5.2, 5.4, 5.6)].

Manage patients with symptomatic and supportive care following an NSAID overdosage. There are no specific antidotes. Consider emesis and/or activated charcoal (60 to 100 grams in adults, 1 to 2 grams per kg of body weight in pediatric patients) and/or osmotic cathartic in symptomatic patients seen within four hours of ingestion or in patients with a large overdosage (5 to 10 times the recommended dosage). Forced diuresis, alkalinization of urine, hemodialysis, or hemoperfusion may not be useful due to high protein binding.

For additional information about overdosage treatment contact a poison control center (1-800-222-1222).

Anaphylactic reactions have been reported with therapeutic ingestion of NSAIDs, and may occur following an overdose.

11 DESCRIPTION

CAMBIA (diclofenac potassium) for oral solution is a nonsteroidal anti-inflammatory drug, available as a buffered soluble powder, designed to be mixed with water prior to oral administration. CAMBIA is a white to off-white, buffered, flavored powder for oral solution packaged in individual unit dose packets.

The chemical name is 2-[(2,6-dichlorophenyl)amino] benzeneacetic acid monopotassium salt. The molecular weight is 334.25. Its molecular formula is C14H10Cl2NKO2, and it has the following structure.

The inactive ingredients in CAMBIA include: flavoring agents (anise and mint), glycerol behenate, mannitol, potassium bicarbonate, and sucralose.

12 CLINICAL PHARMACOLOGY

12.1 Mechanism of Action

CAMBIA has analgesic, anti-inflammatory, and antipyretic properties.

The mechanism of action of CAMBIA, like that of other NSAIDs, is not completely understood but involves inhibition of cyclooxygenase (COX-1 and COX-2).

Diclofenac is a potent inhibitor of prostaglandin synthesis in vitro. Diclofenac concentrations reached during therapy have produced in vivo effects. Prostaglandins sensitize afferent nerves and potentiate the action of bradykinin in inducing pain in animal models. Prostaglandins are mediators of inflammation. Because diclofenac is an inhibitor of prostaglandin synthesis, its mode of action may be due to a decrease of prostaglandins in peripheral tissues.

12.3 Pharmacokinetics

Absorption

Diclofenac is 100% absorbed after oral administration compared to intravenous administration as measured by urine recovery. However, due to first-pass metabolism, only about 50% of the absorbed dose is systemically available. In fasting volunteers, measurable plasma levels were observed within 5 minutes of dosing with CAMBIA. Peak plasma levels were achieved at approximately 0.25 hour in fasting normal volunteers, with a range of 0.17 to 0.67 hours. High fat food had no significant effect on the extent of diclofenac absorption, but there was a reduction in peak plasma levels of approximately 70% after a high fat meal. Decreased Cmax may be associated to decreased effectiveness.

Distribution

The apparent volume of distribution (V/F) of diclofenac potassium is 1.3 L/kg.

Diclofenac is more than 99% bound to human serum proteins, primarily to albumin. Serum protein binding is constant over the concentration range (0.15-105 µg/mL) achieved with recommended doses.

Elimination

Metabolism

Five diclofenac metabolites have been identified in human plasma and urine. The metabolites include 4’-hydroxy-, 5-hydroxy-, 3’-hydroxy-, 4’,5-dihydroxy- and 3’-hydroxy-4’-methoxy diclofenac. The major diclofenac metabolite, 4’-hydroxydiclofenac, has very weak pharmacologic activity. The formation of 4’-hydroxy diclofenac is primarily mediated by CPY2C9. Both diclofenac and its oxidative metabolites undergo glucuronidation or sulfation followed by biliary excretion. Acylglucuronidation mediated by UGT2B7 and oxidation mediated by CPY2C8 may also play a role in diclofenac metabolism. CYP3A4 is responsible for the formation of minor metabolites, 5-hydroxy and 3’-hydroxy- diclofenac. In patients with renal impairment, peak concentrations of metabolites 4’-hydroxy-and 5- hydroxydiclofenac were approximately 50% and 4% of the parent compound after single oral dosing compared to 27% and 1% in normal healthy subjects.

Excretion

Diclofenac is eliminated through metabolism and subsequent urinary and biliary excretion of the glucuronide and the sulfate conjugates of the metabolites. Little or no free unchanged diclofenac is excreted in the urine. Approximately 65% of the dose is excreted in the urine and approximately 35% in the bile as conjugates of unchanged diclofenac plus metabolites. Because renal elimination is not a significant pathway of elimination for unchanged diclofenac, dosing adjustment in patients with mild to moderate renal dysfunction is not necessary. The terminal half-life of unchanged diclofenac is approximately 2 hours.

Specific Populations

Race: There are no pharmacokinetic differences due to race.

Hepatic Impairment: The liver metabolizes almost 100% of diclofenac; there is insufficient information available to support dosing recommendations for CAMBIA in patients with hepatic insufficiency [see Warnings and Precautions (5.3) and Use in Specific Populations (8.6)].

Renal Impairment: In patients with renal impairment (inulin clearance 60-90, 30-60, and <30 mL/min; N=6 in each group), AUC values and elimination rate were comparable to those in healthy subjects [see Warnings and Precautions (5.6) and Use in Specific Populations (8.7)].

Drug Interaction Studies

Aspirin: When NSAIDs were administered with aspirin, the protein binding of NSAIDs were reduced, although the clearance of free NSAID was not altered. The clinical significance of this interaction is not known. See Table 2 for clinically significant drug interactions of NSAIDs with aspirin [see Drug Interactions (7)].

13 NONCLINICAL TOXICOLOGY

13.1 Carcinogenesis, Mutagenesis, and Impairment of Fertility

Carcinogenesis
Long term carcinogenicity studies in rats given diclofenac sodium up to 2 mg/kg/day (less than the recommended human dose [RHD] of 50 mg/day on a body surface area [mg/m^2] basis) have revealed no significant increases in tumor incidence. There was a slight increase in benign mammary fibroadenomas in mid- dose treated (0.5 mg/kg/day or 3 mg/m^2/day) female rats (high-dose females had excessive mortality), but the increase was not significant for this common rat tumor. A 2-year carcinogenicity study conducted in mice employing diclofenac sodium at doses up to 0.3 mg/kg/day (less than the RHD on a mg/m^2 basis) in males and 1 m/kg/day (less than the RHD on a mg/m^2 basis) in females did not reveal any oncogenic potential.

Mutagenesis
Diclofenac sodium was not genotoxic in in vitro (reverse mutation in bacteria [Ames], mouse lymphoma tk) or in in vivo (including dominant lethal and male germinal epithelial chromosomal aberration in Chinese hamster) assays.

Impairment of Fertility
Diclofenac sodium administered to male and female rats at 4 mg/kg/day (less than the RHD on a mg/m^2 basis) did not affect fertility.

14 CLINICAL STUDIES

The efficacy of CAMBIA in the acute treatment of migraine headache was demonstrated in two randomized, double-blind, placebo-controlled trials.

Patients enrolled in these two trials were predominantly female (85%) and white (86%), with a mean age of 40 years (range: 18 to 65). Patients were instructed to treat a migraine of moderate to severe pain with 1 dose of study medication. Patients evaluated their headache pain 2 hours later. Associated symptoms of nausea, photophobia, and phonophobia were also evaluated. In addition, the proportion of patients who were “sustained pain free”, defined as a reduction in headache severity from moderate or severe pain to no pain at 2 hours post- dose without a return of mild, moderate, or severe pain and no use of rescue medication for 24 hours post-dose, was also evaluated. In these studies, the percentage of patients achieving pain freedom 2 hours after treatment and sustained pain freedom from 2 to 24 hours post-dose was significantly greater in patients who received CAMBIA compared with those who received placebo (see Table 3). The percentage of patients achieving pain relief 2 hours after treatment (defined as a reduction in headache severity from moderate or severe pain to mild or no pain) was also significantly greater in patients who received CAMBIA compared with those who received placebo (see Table 3).

Table 3: Percentage of Patients with 2-Hour Pain Freedom, Sustained Pain Freedom 2-24 Hours, and 2-Hour Pain Relief Following Treatment
Study 1 | CAMBIA (n=265) | Placebo (n=257)
2-Hour Pain Free | 24% | 13%
2-24h Sustained Pain Free | 22% | 10%
2-Hour Pain Relief | 48% | 27%
Study 2 | CAMBIA (n=343) | Placebo (n=347)
2-Hour Pain Free | 25% | 10%
2-24h Sustained Pain Free | 19% | 7%
2-Hour Pain Relief | 65% | 41%

The estimated probability of achieving migraine headache pain freedom within 2 hours following treatment with CAMBIA is shown in Figure 1.

Figure 1. Percentage of Patients with Initial Headache Pain Freedom within 2 Hours

There was a decreased incidence of nausea, photophobia and phonophobia following administration of CAMBIA, compared to placebo. The efficacy and safety of CAMBIA was unaffected by age or gender of the patient.

16 HOW SUPPLIED/STORAGE AND HANDLING

CAMBIA (diclofenac potassium) 50 mg, is a white to off-white, buffered, flavored powder for oral solution, supplied as one or more sets of three perforated co-joined individual dose packets. Each individual packet is designed to deliver a dose of 50 mg diclofenac potassium when mixed in water.

NDC 13913-012-01 Individual CAMBIA Packets
NDC 13913-012-03 Boxes of nine (9) CAMBIA Packets

Storage

Store at 25°C (77°F). Excursions permitted from 15°C-30°C (59°F-86°F). [See USP Controlled Room Temperature]

17 PATIENT COUNSELING INFORMATION

Advise the patient to read the FDA-approved patient labeling (Medication Guide) that accompanies each prescription dispensed. Inform patients, families, or their caregivers of the following information before initiating therapy with CAMBIA and periodically during the course of ongoing therapy.

Cardiovascular Thrombotic Events
Advise patients to be alert for the symptoms of cardiovascular thrombotic events, including chest pain, shortness of breath, weakness, or slurring of speech, and to report any of these symptoms to their health care provider immediately [see Warnings and Precautions (5.1)].

Gastrointestinal Bleeding, Ulceration, and Perforation
CAMBIA, like other NSAIDS, can cause GI discomfort and more serious GI adverse events such as ulcers and bleeding, which may result in hospitalization and even death. Inform patients of the increased risk, and advise patients to report symptoms of ulcerations and bleeding, including epigastric pain, dyspepsia, melena, and hematemesis to their health care provider. Inform patients of the importance of follow-up in the setting of concomitant use of low-dose aspirin for cardiac prophylaxis [see Warnings and Precautions (5.2)].

Hepatotoxicity

Inform patients of the warning signs and symptoms of hepatotoxicity (e.g., nausea, fatigue, lethargy, pruritus, diarrhea, jaundice, right upper quadrant tenderness, and “flu-like” symptoms). If these occur, instruct patients to stop CAMBIA and seek immediate medical therapy [see Warnings and Precautions (5.3)].

Heart Failure and Edema
Advise patients to be alert for the symptoms of congestive heart failure including shortness of breath, unexplained weight gain, or edema and to contact their healthcare provider if such symptoms occur [see Warnings and Precautions (5.5)].

Anaphylactic Reactions
Inform patients of the signs of an anaphylactic reaction (e.g., difficulty breathing, swelling of the face or throat). Instruct patients to seek immediate emergency help if these occur [see Contraindications (4) and Warnings and Precautions (5.7)].

Serious Skin Reactions, Including DRESS
Advise patients to stop taking CAMBIA immediately if they develop any type of rash, blisters, fever or other signs of hypersensitivity such as itching and to contact their healthcare provider as soon as possible. CAMBIA, like other NSAIDS, can cause serious skin reactions such as exfoliative dermatitis, Stevens-Johnson syndrome (SJS), toxic epidermal necrosis (TEN), and DRESS, which may result in hospitalizations and even death [see Warnings and Precautions (5.9, 5.10)].

Medication Overuse Headache
Inform patients that use of acute migraine drugs for 10 or more days per month may lead to an exacerbation of headache and encourage patients to record headache frequency and drug use (e.g., by keeping a headache diary) [see Warnings and Precautions (5.11)].

Fetal Toxicity
Inform pregnant women to avoid use of CAMBIA and other NSAIDs starting at 30 weeks gestation because of the risk of the premature closing of the fetal ductus arteriosus. If treatment with CAMBIA is needed for a pregnant woman between about 20 to 30 weeks gestation, advise her that she may need to be monitored for oligohydramnios, if treatment continues for longer than 48 hours [see Warnings and Precautions (5.12) and Use in Specific Populations (8.1)].

Lactation

Advise patients to notify their healthcare provider if they are breastfeeding or plan to breastfeed [see Use in Specific Populations (8.2)].

Female Fertility
Advise females of reproductive potential who desire pregnancy that NSAIDs, including CAMBIA, may delay or prevent rupture of ovarian follicles, which has been associated with reversible infertility in some women [see Use in Specific Populations (8.3)].

Avoid Concomitant Use of NSAIDs
Inform patients that the concomitant use of CAMBIA with other NSAIDs or salicylates (e.g., diflunisal, salsalate) is not recommended due to the increased risk of gastrointestinal toxicity, and little or no increase in efficacy [see Warnings and Precautions (5.2) and Drug Interactions (7)]. Alert patients that NSAIDs may be present in “over the counter” medications for treatment of colds, fever, or insomnia.

Use of NSAIDS and Low-Dose Aspirin
Inform patients not to use low-dose aspirin concomitantly with CAMBIA until they talk to their healthcare provider [see Drug Interactions (7)].

Distributed by:

Assertio Therapeutics, Inc.
100 South Saunders Road
Lake Forest, IL 60045
United States of America

Manufactured and Distributed Under License from APR Applied Pharma Research SA, Balerna, Switzerland

U.S. Patents: 6,974,595; 7,482,377; 7,759,394; 8,097,651

CAM-003-C.8

©2024 Assertio Therapeutics, Inc.

Medication Guide
CAMBIA (Cam-bē-ǝ or Cam-bē-a)
(diclofenac potassium)
for oral solution

What is the most important information I should know about Cambia?

CAMBIA contains diclofenac (a non-steroidal anti-inflammatory drug or NSAID).

NSAIDs, including CAMBIA, can cause serious side effects, including:

- Increased risk of a heart attack or stroke that can lead to death.This risk may happen early in treatment and may increase:
  - with increasing doses of NSAIDs
  - with longer use of NSAIDs

Do not take NSAIDs, including CAMBIA, right before or after a heart surgery called a “coronary artery bypass graft (CABG)."

Avoid taking NSAIDs, including CAMBIA, after a recent heart attack, unless your healthcare provider tells you to. You may have an increased risk of another heart attack if you take NSAIDs after a recent heart attack.

- Increased risk of bleeding, ulcers, and tears (perforation) of the esophagus (tube leading from the mouth to the stomach), stomach and intestines:
  - anytime during use
  - without warning symptoms
  - that may cause death

- The risk of getting an ulcer or bleeding increases with:
  - past history of stomach ulcers, or stomach or intestinal bleeding with use of NSAIDs
  - taking medicines called “corticosteroids”, “anticoagulants”, “SSRIs”, or “SNRIs”
  - increasing doses of NSAIDs
  - older age
  - longer use of NSAIDs
  - poor health
  - smoking
  - advanced liver disease
  - drinking alcohol
  - bleeding problems

- CAMBIA should only be used:
  - exactly as prescribed
  - at the lowest dose possible for your treatment
  - for the shortest time needed

What is CAMBIA?

CAMBIA is a prescription medicine used to treat migraine attacks in adults. It does not prevent or lessen the number of migraines you have, and it is not for other types of headaches. CAMBIA contains diclofenac potassium (a non-steroidal anti-inflammatory drug or NSAID).

How should I take CAMBIA?

Take CAMBIA exactly as your healthcare provider tells you to take it.

Take 1 dose of CAMBIA to treat your migraine headache:

- remove one single dose packet from a set of three packets
- open packet only when you are ready to use it
- empty contents of packet into 1 to 2 ounces (30 to 60 mL) of water
- mix well and drink the water and powder mixture
- throw away empty packet in a safe place and out of the reach of children.
- taking CAMBIA with food may cause a reduction in effectiveness compared to taking CAMBIA on an empty stomach
- do not take more CAMBIA than directed by your healthcare provider. In case of overdose, get medical help or contact a Poison Control Center right away

Who should not take CAMBIA?

Do not take CAMBIA:

- if you have had an asthma attack, hives, or other allergic reaction with aspirin, diclofenac, or any other NSAIDs.
- right before or after heart bypass surgery.

Before taking CAMBIA, tell your healthcare provider about all of your medical conditions, including if you:

- have liver or kidney problems
- have a history of stomach ulcer or bleeding in your stomach or intestines
- have any allergies to any medicines
- have chest pain, shortness of breath, irregular heartbeats
- have high blood pressure
- have asthma
- are pregnant, think you might be pregnant, or are trying to become pregnant. Taking NSAIDs, including CAMBIA, at about 20 weeks of pregnancy or later may harm your unborn baby. If you need to take NSAIDs for more than 2 days when you are between 20 and 30 weeks of pregnancy, your healthcare provider may need to monitor the amount of fluid in your womb around your baby. You should not take NSAIDs after about 30 weeks of pregnancy.
- are breastfeeding or plan to breastfeed.
- have a headache that is different from your usual migraine

Tell your healthcare provider about all of the medicines you take, including prescription or over-the- counter medicines, vitamins or herbal supplements. NSAIDs, like CAMBIA, and some other medicines can interact with each other and cause serious side effects. Do not start taking any new medicine without talking to your healthcare provider first.

Especially tell your doctor if you take:

- aspirin
- any anticoagulant medicines (warfarin, Coumadin, Jantoven)

Know the medicines you take. Keep a list of your medicines and show it to your doctor and pharmacist when you get a new medicine.

What are the possible side effects of CAMBIA?

CAMBIA can cause serious side effects, including:

See “What is the most important information I should know about CAMBIA?”

- new or worse high blood pressure
- heart failure
- liver problems including liver failure
- kidney problems including kidney failure
- bleeding and ulcers in the stomach and intestine
- low red blood cells (anemia)
- life-threatening skin reactions
- life-threatening allergic reactions
- asthma attacks in people who have asthma
- medication overuse headaches. Some people who use too much CAMBIA may have worse headaches (medication overuse headache). If your headaches get worse, your healthcare provider may decide to stop your treatment with CAMBIA.

• Other side effects of NSAIDs include: stomach pain, constipation, diarrhea, gas, heartburn, nausea, vomiting, and dizziness.

Get emergency help right away if you get any of the following symptoms:

- shortness of breath or trouble breathing
- chest pain
- weakness in one part or side of your body
- slurred speech
- swelling of the face or throat

Stop taking CAMBIA and call your healthcare provider right away if you get any of the following symptoms

- nausea that seems out of proportion to your migraine
- sudden or severe pain in your belly
- more tired or weaker than usual
- diarrhea
- itching
- your skin or eyes look yellow
- indigestion or stomach pain
- vomit blood
- there is blood in your bowel movement or it is black and sticky like tar
- unusual weight gain
- more tired or weaker than usual
- skin rash or blisters with fever
- swelling of the arms, legs, hands and feet
- flu-like symptoms

If you take too much of your NSAID, call your healthcare provider or get medical help right away.

These are not all the possible side effects of NSAIDs. For more information, ask your healthcare provider or pharmacist about NSAIDs.

Call your doctor for medical advice about side effects. You may report side effects to FDA at 1-800-FDA-1088.

Other information about NSAIDs

- Aspirin is an NSAID but it does not increase the chance of a heart attack. Aspirin can cause bleeding in the brain, stomach, and intestines. Aspirin can also cause ulcers in the stomach and intestines.
- Some NSAIDs are sold in lower doses without a prescription (over-the counter). Talk to your healthcare provider before using over-the-counter NSAIDs for more than 10 days.

General information about the safe and effective use of NSAIDs

Medicines are sometimes prescribed for purposes other than those listed in a Medication Guide. Do not use NSAIDs for a condition for which it was not prescribed. Do not give NSAIDs to other people, even if they have the same symptoms that you have. It may harm them.

If you would like more information about NSAIDs, talk with your healthcare provider. You can ask your pharmacist or healthcare provider for information about NSAIDs that is written for health professionals.

Distributed by: Assertio Therapeutics, Inc., 100 South Saunders Road, Lake Forest, IL 60045
For more information go to www.CambiaRx.com or call 1-866-458-6389

This Medication Guide has been approved by the U.S. Food and Drug Administration. Revised 4/2024 CAM-004-C.6